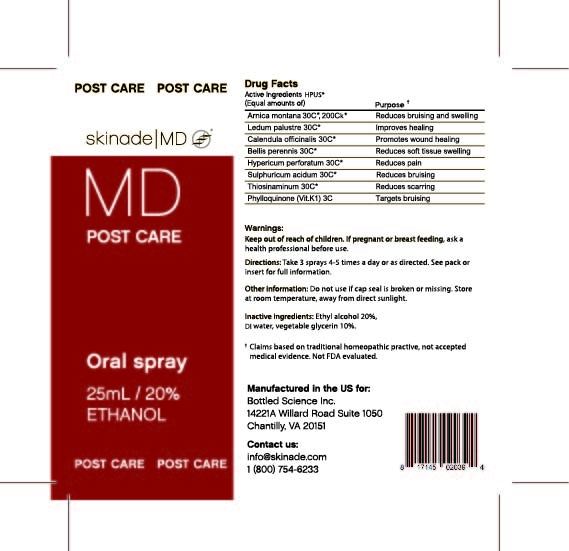 DRUG LABEL: Skinade MD INsupport
NDC: 73130-004 | Form: SPRAY
Manufacturer: Bottled Science, Inc.
Category: homeopathic | Type: HUMAN OTC DRUG LABEL
Date: 20251016

ACTIVE INGREDIENTS: ARNICA MONTANA 30 [hp_C]/1 mL; LEDUM PALUSTRE WHOLE 30 [hp_C]/1 mL; CALENDULA OFFICINALIS FLOWER 30 [hp_C]/1 mL; HYPERICUM PERFORATUM FLOWER 30 [hp_C]/1 mL; BELLIS PERENNIS 30 [hp_C]/1 mL; SULFURIC ACID 30 [hp_C]/1 mL; ALLYLTHIOUREA 30 [hp_C]/1 mL; PHYLLOQUINONE OMEGA-HYDROXYLASE CYP4F11 3 [hp_C]/1 mL
INACTIVE INGREDIENTS: GLYCERIN; ALCOHOL; WATER

MD INsupport

Drug Facts

Contains 0.25% of each of the following HPUS ingredients:

Active Ingredients | Purpose
Arnica Montana 30C, 200Ck | Reduces bruising and swelling
Ledum Palustre 30C | Improves healing
Calendula Officinalis 30C | Promotes wound healing
Bellis Perennis 30C | Reduces soft tissue swelling
Hypericum Perforatum 30C | Reduces pain
Sulphuricum Acidum 30C | Reduces bruising
Thiosinaminum 30C | Reduces scarring
Phylloquinone (Vit.K1) 3C | Targets bruising

Warnings

Keep out of reach of children. If pregnant or breast feeding, ask a health professional before use.

Directions

Take 3 sprays 4-5 times per day or as directed. See pack or insert for full information

Other Information

Do not use if cap seal is broken or missing. Store at room temperature, away from direct sunlight.

Inactive Ingredients

Ethyl Alcohol 20%, purified water, vegetable glycerin 10%

Indications and Usage

Reduces bruising and swelling, improves healing, promotes wound healing

Purpose

Reduces bruising and swelling

Improves healing

Promotes wound healing

Reduces soft tissue swelling

Reduces pain

Reduces bruising

Reduces scarring

Targets bruising

Warnings

Claims based on traditional Homeopathic practive, not accepted medical evidence. Not FDA evaluated

RECENT MAJOR CHANGES

Dosage updated to recommend consulting Pack or Insert for full information

Indications and Usage section updated

PACKAGE LABEL

Skinade_MD_packaging_Spray bottle label_US_11.11.2025 copy.jpg